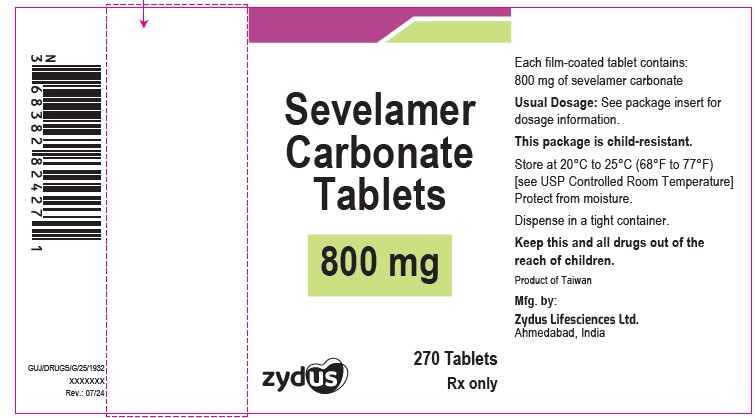 DRUG LABEL: Sevelamer carbonate
NDC: 70771-1520 | Form: TABLET, FILM COATED
Manufacturer: Zydus Lifesciences Limited
Category: prescription | Type: HUMAN PRESCRIPTION DRUG LABEL
Date: 20240812

ACTIVE INGREDIENTS: SEVELAMER CARBONATE 800 mg/1 1
INACTIVE INGREDIENTS: CASTOR OIL; CROSPOVIDONE (15 MPA.S AT 5%); DIBUTYL SEBACATE; FERROSOFERRIC OXIDE; HYPROMELLOSE 2910 (15 MPA.S); HYPROMELLOSE 2910 (5 MPA.S); HYPROMELLOSE 2910 (50 MPA.S); HYPROMELLOSE 2910 (6 MPA.S); LACTOSE MONOHYDRATE; MAGNESIUM STEARATE; MICROCRYSTALLINE CELLULOSE; POLYVINYL ALCOHOL, UNSPECIFIED; POVIDONE K90; PROPYLENE GLYCOL; SHELLAC; SILICON DIOXIDE; TRIACETIN; WATER

Sevelamer Tablets

PACKAGE LABEL.PRINCIPAL DISPLAY PANEL

NDC 70771-1520-8

Sevelamer Tablets, 800 mg

270 Tablets

Rx only